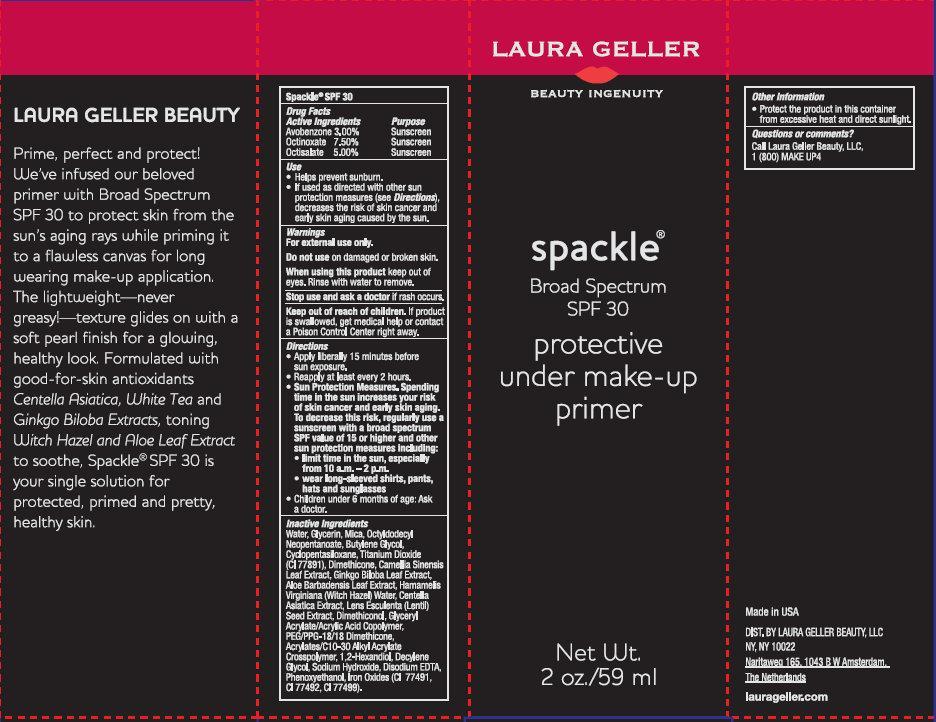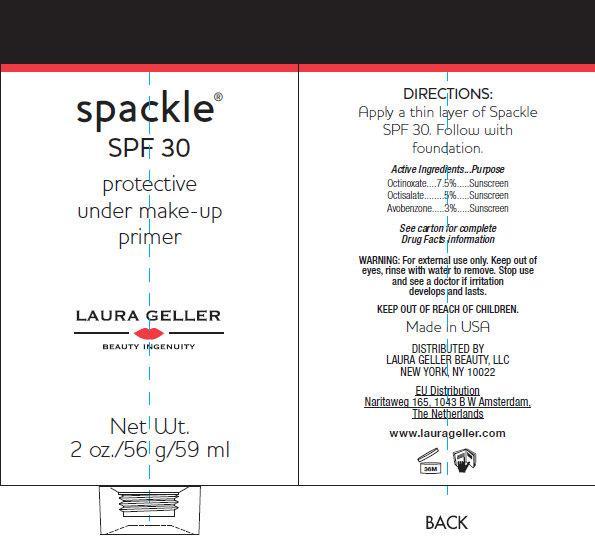 DRUG LABEL: LAURA GELLER spackle Broad Spectrum SPF 30 protective under make-up primer
                
NDC: 51389-210 | Form: CREAM
Manufacturer: Laura Geller Beauty, LLC
Category: otc | Type: HUMAN OTC DRUG LABEL
Date: 20140514

ACTIVE INGREDIENTS: AVOBENZONE 30 mg/1 mL; OCTINOXATE 75 mg/1 mL; OCTISALATE 50 mg/1 mL
INACTIVE INGREDIENTS: WATER; GLYCERIN; MICA; OCTYLDODECYL NEOPENTANOATE; BUTYLENE GLYCOL; CYCLOMETHICONE 5; TITANIUM DIOXIDE; DIMETHICONE; GREEN TEA LEAF; GINKGO; ALOE VERA LEAF; HAMAMELIS VIRGINIANA TOP WATER ; CENTELLA ASIATICA; LENTIL; PEG/PPG-18/18 DIMETHICONE; 1,2-HEXANEDIOL; DECYLENE GLYCOL; SODIUM HYDROXIDE; EDETATE DISODIUM; PHENOXYETHANOL; FERRIC OXIDE RED; FERRIC OXIDE YELLOW; FERROSOFERRIC OXIDE

LAURA GELLER spackle Broad Spectrum SPF 30 protective under make-up primer

LAURA GELLER spackle Broad Spectrum SPF 30 protective under make-up primer

Active Ingredients

Avobenzone 3.00%
Octinoxate 7.50%
Octisalate 5.00%

Purpose

Sunscreen

USES

- Helps prevent sunburn.
- If used as directed with other sun protection measures (see Directions), decreases the risk of skin cancer and early skin aging caused by the sun.

WARNINGS

For external use only.

Do not use

on damaged or broken skin.

When using this product

keep out of eyes. Rinse with water to remove.

Stop use and ask a doctor

if rash occurs.

Keep out of reach of children

If product is swallowed, get medical help or contact a Poison Control Center right away.

DIRECTIONS

- Apply liberally 15 minutes before sun exposure.
- Use a water resistant sunscreen if swimming or sweating.
- Reapply at least every 2 hours.
- Sun Protection Measures. Spending time in the sun increases your risk of skin cancer and early skin aging. To decrease this risk, regularly use a sunscreen with a Broad Spectrum SPF value of 15 or higher and other sun protection measures including:
-
  - limit time in the sun, especially from 10 a.m. - 2 p.m.
  - wear long-sleeved shirts, pants, hats and sunglasses.
- Children under 6 months of age: Ask a doctor.

INACTIVE INGREDIENTS

Water, Glycerin, Mica, Octyldodecyl Neopentanoate, Butylene Glycol, Cyclopentsiloxane, Titanium Dioxide (CI 77891), Dimethicone, Camellia Sinensis Leaf Extract, Ginkgo Biloba Leaf Extract, Aloe Barbadensis Leaf Extract, Hamamelis Virginia (Witch Hazel) Water, Centella Asiatica Extract, Lens Esculenta (Lentil) Seed Extract, Dimethiconol, Glyceryl Acrylate/Acrylic Acid Copolymer, PEG/PPG-18 Dimethicone, Acrylates/C10-30 Alkyl Acrylate Crosspolymer, 1,2-Hexandiol, Decylene Glycol, Sodium Hydroxide, Disodium EDTA, Phenoxyethanol, Iron Oxides (CI 77491, CI 77492, CI 77499).

Other Information

- Protect the product in this container from excessive heat and direct sun.

Questions or comments?

Call Laura Gellar Beauty, LLC, 1 (800) MAKE UP4